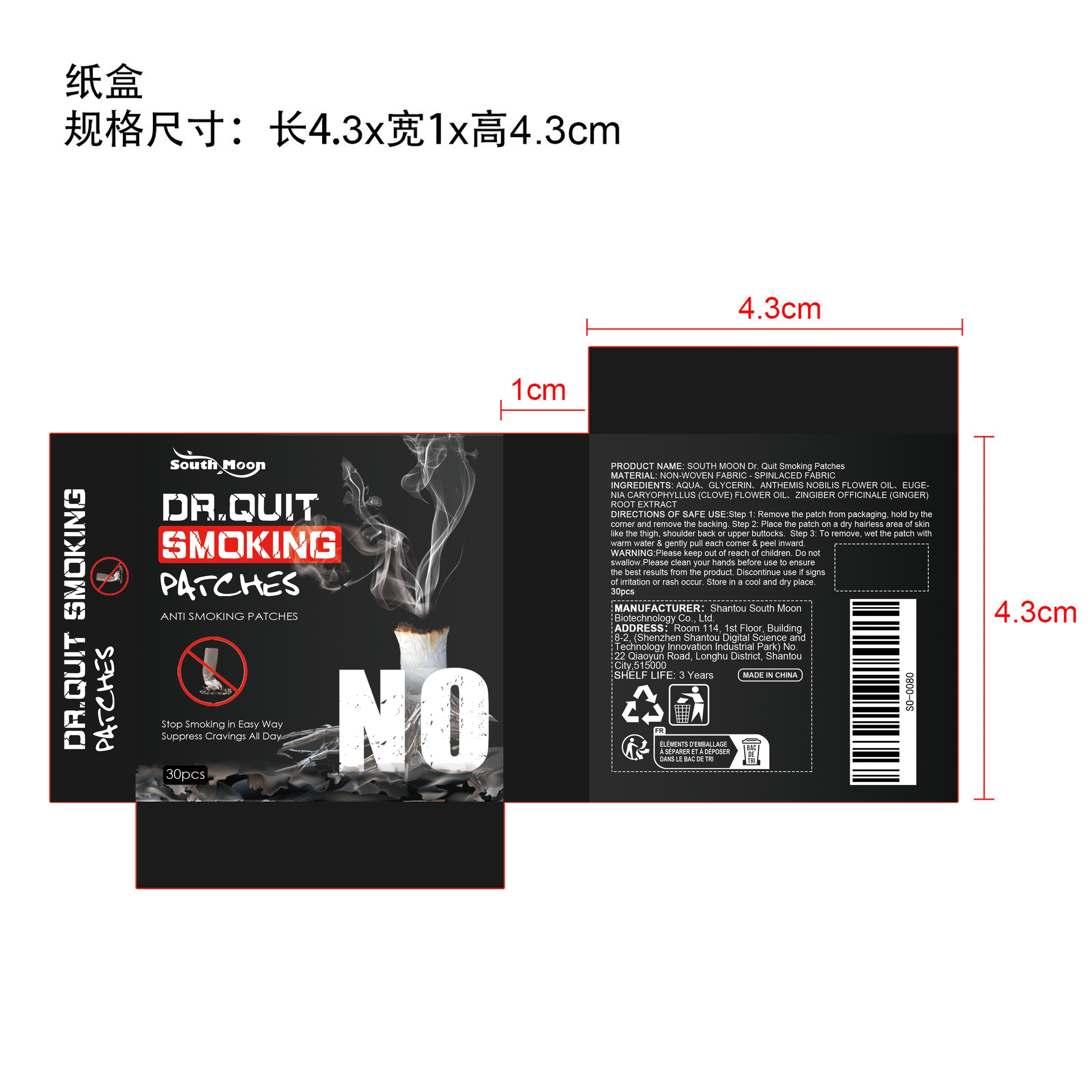 DRUG LABEL: SOUTH MOON Dr. Quit Smoking Patches
NDC: 84983-021 | Form: PATCH
Manufacturer: Shantou South Moon Biotechnology Co., Ltd.
Category: otc | Type: HUMAN OTC DRUG LABEL
Date: 20260126

ACTIVE INGREDIENTS: ANTHEMIS NOBILIS FLOWER OIL 0.015 mg/30 mg; EUGENIA CARYOPHYLLUS (CLOVE) FLOWER OIL 0.015 mg/30 mg; ZINGIBER OFFICINALE (GINGER) ROOT OIL 0.015 mg/30 mg
INACTIVE INGREDIENTS: GLYCERIN 0.3 mg/30 mg; AQUA 29.655 mg/30 mg

ACTIVE INGREDIENT

ANTHEMIS NOBILIS FLOWER OIL、EUGENIA CARYOPHYLLUS (CLOVE) FLOWER OIL、ZINGIBER OFFICINALE (GINGER) ROOT EXTRACT

PURPOSE

1. Through slow-release penetration, the active ingredients are gradually released, which effectively helps relieve fatigue caused by quitting smoking, restores physical vitality, and promotes overall health. 2. Designed specifically for quitting smoking, it helps alleviate the discomfort caused by quitting smoking, relaxes the body and mind, and improves the success rate of quitting smoking. 3. Help the body gradually adapt to a smoke-free life and promote a healthy lifestyle.

WHEN USING

1. Remove the patch from packaging, hold by the corner and remove the backing.

2.Place the patch on a dry hairless area of skin like the thigh, shoulder back or upper buttocks.

3.To remove, wet the patch with warm water & gently pull each corner & peel inward.

WARNINGS

Please keep out of reach of children. Do not swallow.Please clean your hands before use to ensure the best results from the product. Discontinue use if signs of irritation or rash occur. Store in a cool and dry place.

DO NOT USE

Discontinue use if signs of irritation or rash occur.

STOP USE

Discontinue use if signs of irritation or rash occur.

KEEP OUT OF REACH OF CHILDREN

Please keep out of reach of children. Do not swallow.

STORAGE AND HANDLING

Store in a cool and dry place.

INACTIVE INGREDIENT

AQUA、GLYCERIN

INDICATIONS AND USAGE

1. Remove the patch from packaging, hold by the corner and remove the backing.

2.Place the patch on a dry hairless area of skin like the thigh, shoulder back or upper buttocks.

3.To remove, wet the patch with warm water & gently pull each corner & peel inward.

DOSAGE AND ADMINISTRATION

1. Remove the patch from packaging, hold by the corner and remove the backing.

2.Place the patch on a dry hairless area of skin like the thigh, shoulder back or upper buttocks.

3.To remove, wet the patch with warm water & gently pull each corner & peel inward.